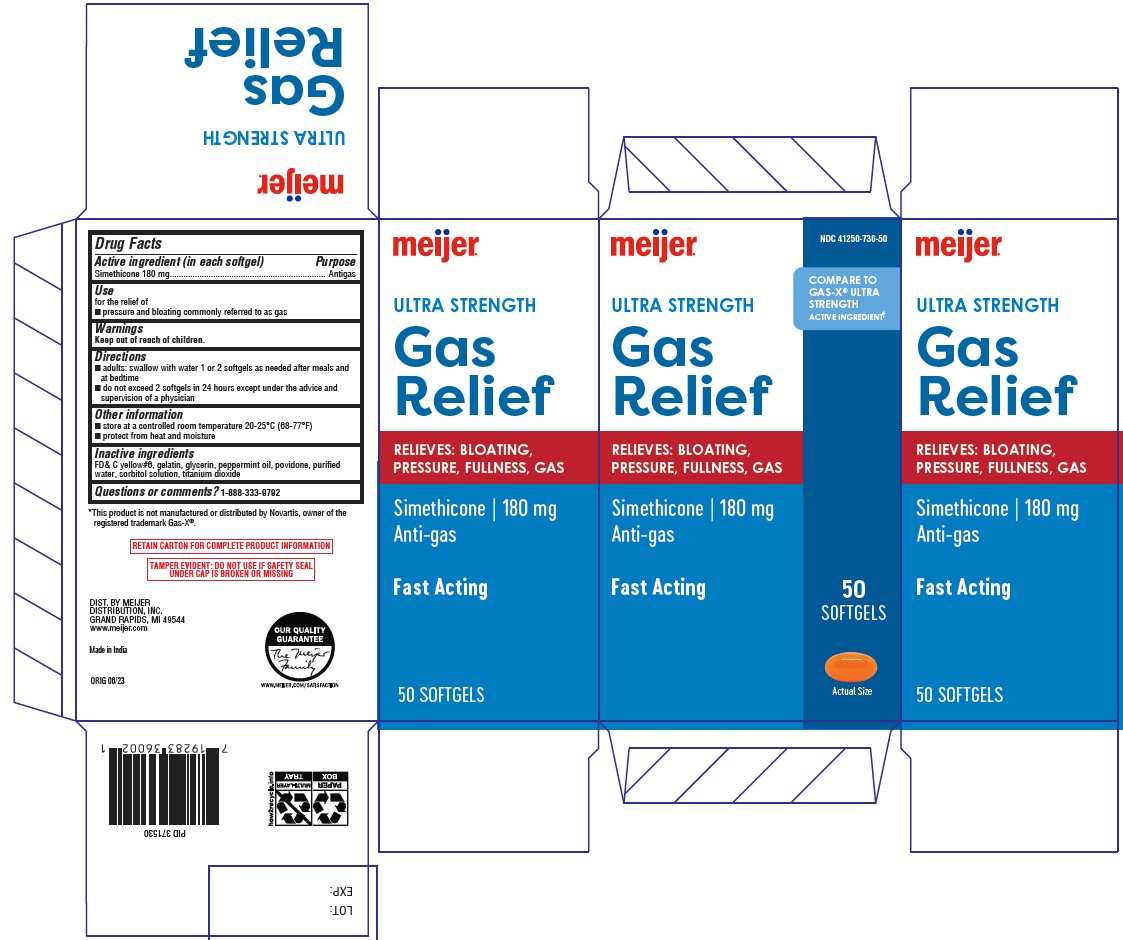 DRUG LABEL: Ultra Strength Gas Relief
NDC: 79481-0037 | Form: CAPSULE, LIQUID FILLED
Manufacturer: Meijer Distribution Inc.
Category: otc | Type: HUMAN OTC DRUG LABEL
Date: 20241220

ACTIVE INGREDIENTS: DIMETHICONE 180 mg/1 1
INACTIVE INGREDIENTS: FD&C YELLOW NO. 6; GELATIN; GLYCERIN; PEPPERMINT OIL; POVIDONE K30; WATER; SORBITOL SOLUTION; TITANIUM DIOXIDE

Meijer Ultra Strength Gas Relief

Drug Facts

Uses

for the relief of
■ pressure and bloating commonly referred to as gas

Warnings

Keep out of reach of children.

Keep out of reach of children.

Questions or comments? 1-888-333-9792

PRINCIPAL DISPLAY PANEL

Compare to the active

ingredient in Gas-X®

Ultra Strength Softgels*

Simethicone 180mg

Anti-gas

Fast Relief of:

Bloating

Pressure

Fullness

Gas

Easy to swallow softgels

50 Softgels